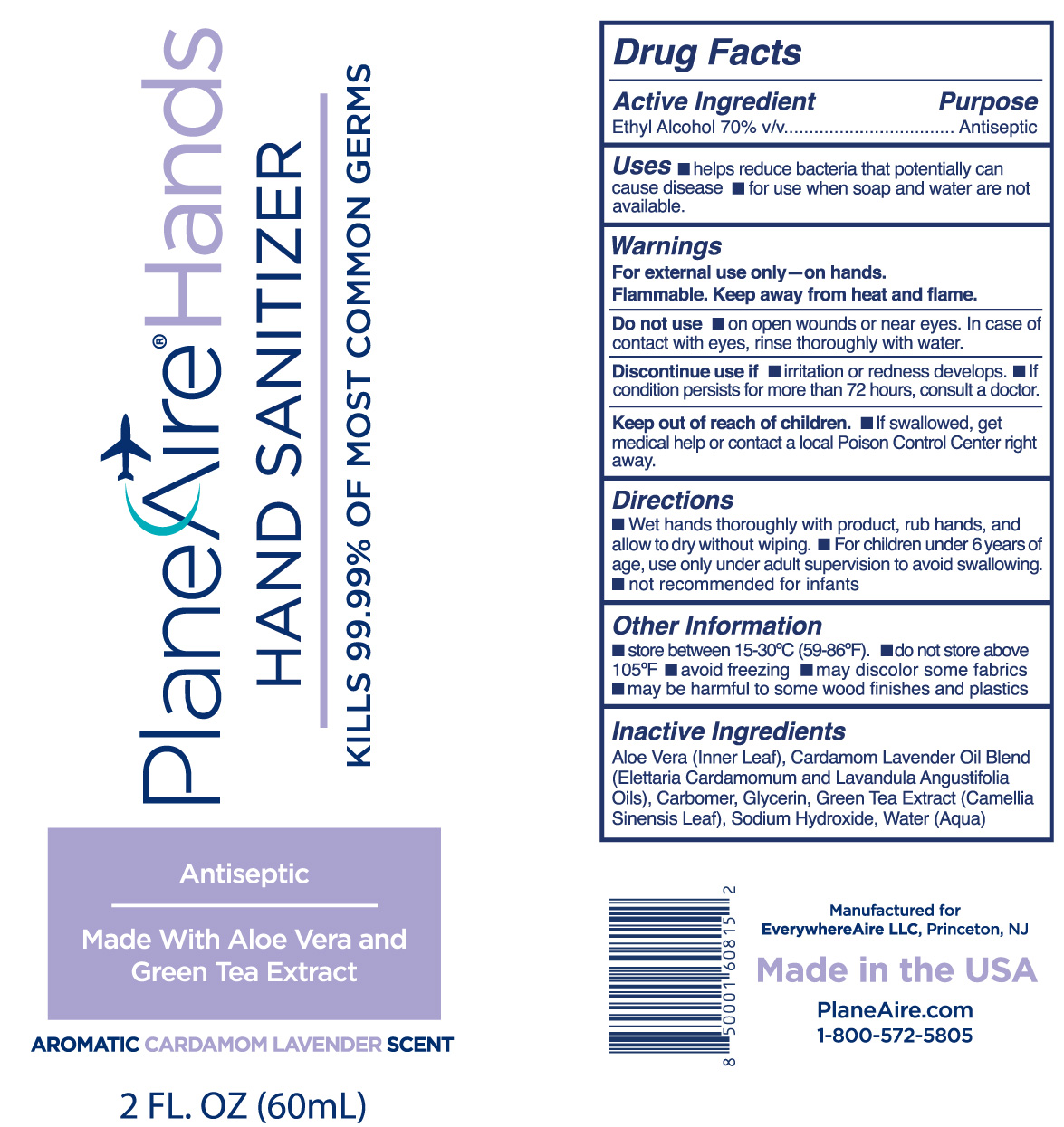 DRUG LABEL: PlaneAire Hands Hand Sanitizer
NDC: 80335-110 | Form: GEL
Manufacturer: EverywhereAire LLC
Category: otc | Type: HUMAN OTC DRUG LABEL
Date: 20211007

ACTIVE INGREDIENTS: ALCOHOL 70 mL/100 mL
INACTIVE INGREDIENTS: GLYCERIN; WATER; GREEN TEA LEAF; SODIUM HYDROXIDE; CARBOMER 980; ALOE VERA LEAF POLYSACCHARIDES; CARDAMOM OIL; LAVENDER OIL

PlaneAire Hands gel Cardamom Lavender hand sanitizer

Active Ingredient(s)

Alcohol 70% v/v.

Purpose

Antiseptic

Use

Hand Sanitizer to help reduce bacteria that potentially can cause disease. For use when soap and water are not available.

Warnings

For external use only on hands. Flammable. Keep away from heat and flame

Do not use

- on open wounds or near eyes. In case of contact with eyes, rinse thoroughly with water.

When using this product keep out of eyes and wounds. In case of contact with eyes, rinse eyes thoroughly with water.
Keep out of reach of children. If swallowed, get medical help or contact a Poison Control Center right away.

STOP USE

Doscontinue use if irritation or rash develops. If condition persists for more than 72 hours, consult a doctor.

Keep out of reach of children. If swallowed, get medical help or contact a Poison Control Center right away.

Directions

- Wet hands thoroughly with product, rub hands, and allow to dry without wiping.
- For children under 6 years of age, use only under adult supervision to avoid swallowing
- Not recommended for infants

Other information

- Store between 15-30C (59-86F)
- Do not store above 105F
- Avoid freezing
- may discolor some fabrics
- may be harmful to some wood finishes and plastics

Inactive ingredients

aloe vera, green tea, glycerin,carbomer, cardamom oil, lavender oil, sodium hydroxide, water

Directions

- Wet hands thoroughly with product, rub hands, and allow to dry without wiping.
- For children under 6 years of age, use only under adult supervision to avoid swallowing
- Not recommended for infants

Package Label - Principal Display Panel

60 mL NDC: 80335-110-02